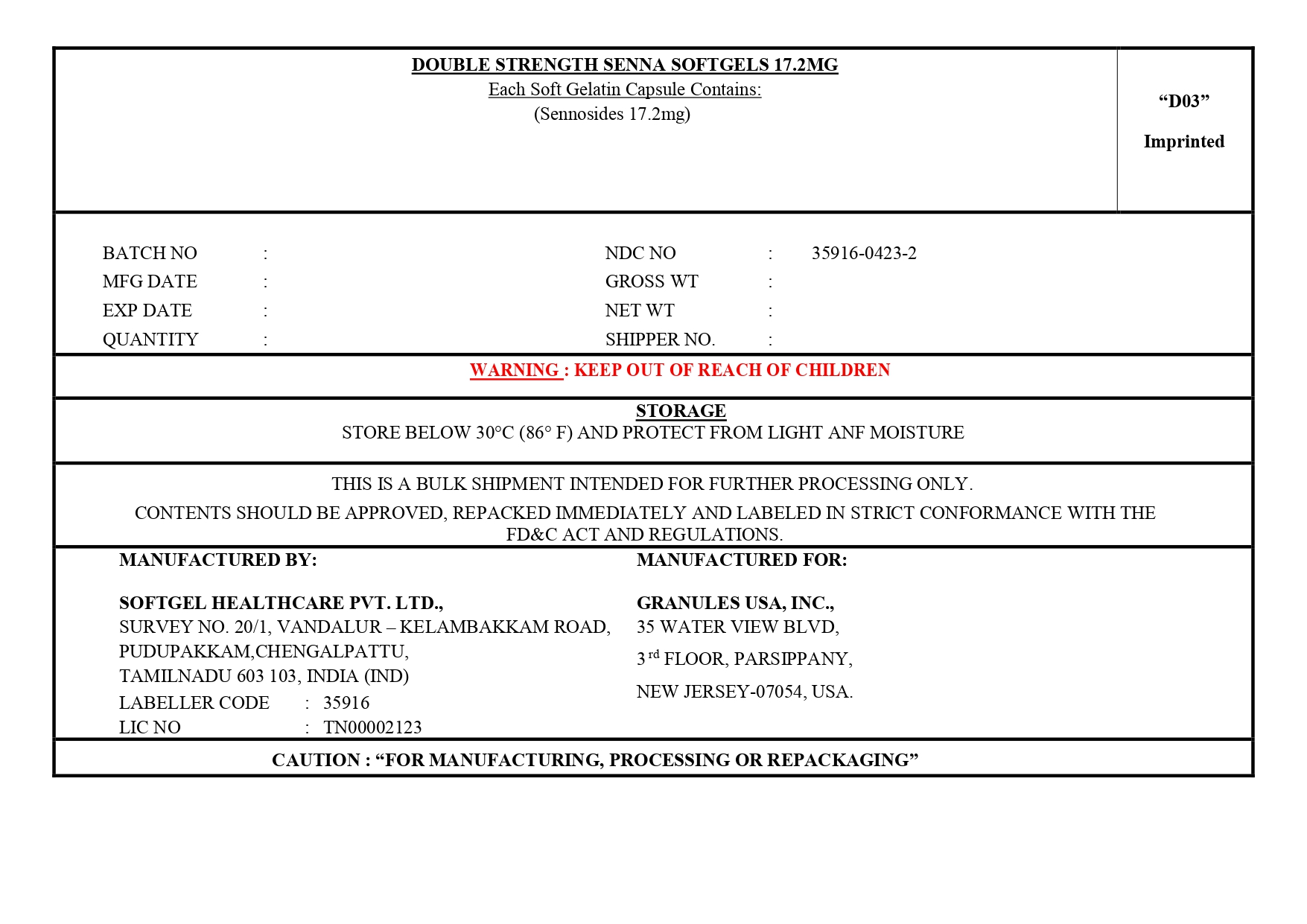 DRUG LABEL: Sennosides
NDC: 35916-0423 | Form: CAPSULE, LIQUID FILLED
Manufacturer: SOFTGEL HEALTHCARE PRIVATE LIMITED
Category: otc | Type: HUMAN OTC DRUG LABEL
Date: 20260127

ACTIVE INGREDIENTS: SENNOSIDES 17.2 mg/1 1
INACTIVE INGREDIENTS: WATER; GLYCERIN; LECITHIN, SOYBEAN; METHYLPARABEN; FUMARIC ACID; TITANIUM DIOXIDE; FD&C RED NO. 40; SORBITOL; FD&C BLUE NO. 1; GELATIN; FD&C YELLOW NO. 6; FD&C BLUE NO. 2; YELLOW WAX; SOYBEAN OIL

Sennosides 17.2 mg Softgels (Senna)

Actice ingredient

(in each softgel)
Sennosides 17.2 mg

Purpose

Laxative

Uses

- relieves occasional constipation (irregularity)
- generally produces a bowel movement within 6-12 hours

Do not use

■ laxative products for longer than 1 week unless directed by a doctor

Ask a doctor before use if you have

■ stomach pain
■ nausea
■ vomiting
■ noticed a sudden change in bowel habits that continues over a period of 2 weeks

Stop use and consult a doctor if

you have rectal bleeding or fail to have a bowel movement after use of a laxative. These may indicate a serious condition.

If pregnant or breast-feeding,

ask a health professional before use.

Keep out of reach of children

In case of overdose, get medical help or contact a Poison Control Center right away

Directions

- take preferably at bedtime or as directed by a doctor adults and children 12 years and over
- 1 capsule once a day. Maximum 2 capsules twice a day. children 6 to under 12 years
- maximum 1 capsule twice a day children under 6 years
- ask a doctor

Other Information

store below 30°C (86°F) and protect from light and moisture

Inactive ingredients

FD&C blue no.1, FD&C blue no.2, FD&C red no. 40, FD&C yellow no.6, fumaric acid, gelatin, glycerol, lecithin, liquid sorbitol, methyl hydroxy benzoate, purified water, refined soya oil, titanium dioxide, yellow bees wax.

Questions or comments?

call 1-877-770-3183: weekdays 9:00 AM to 4:30 PM EST